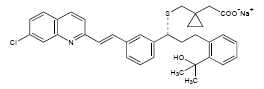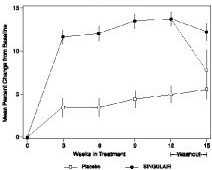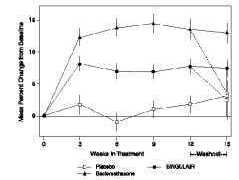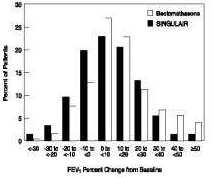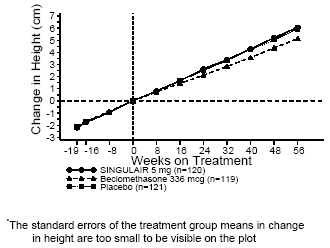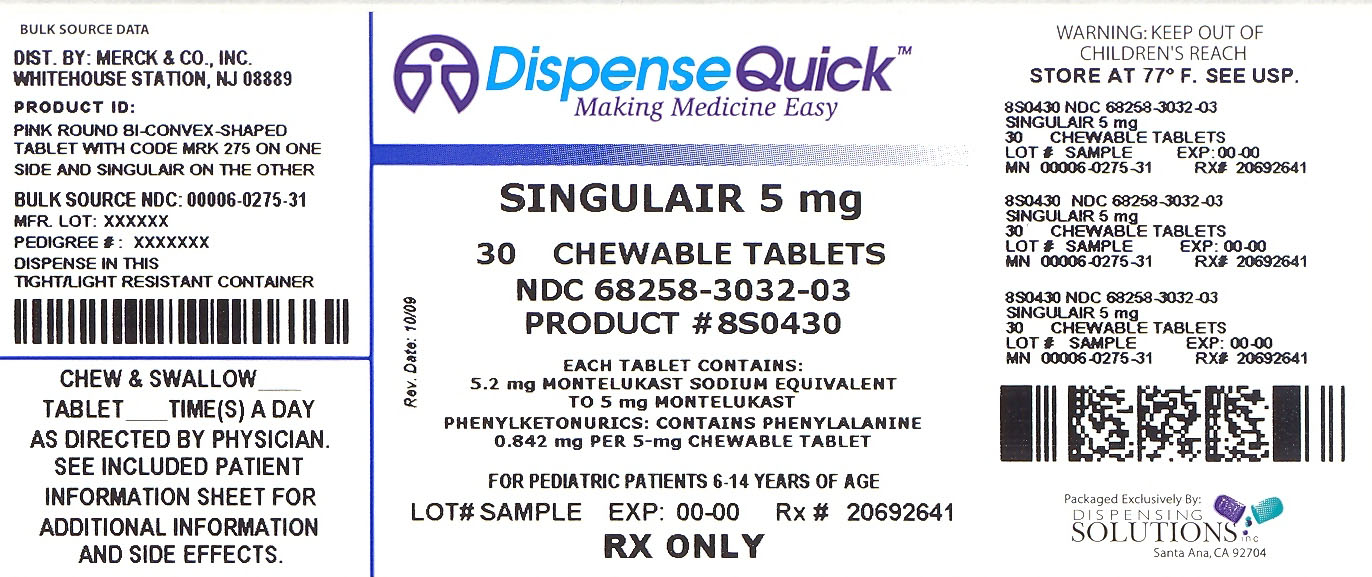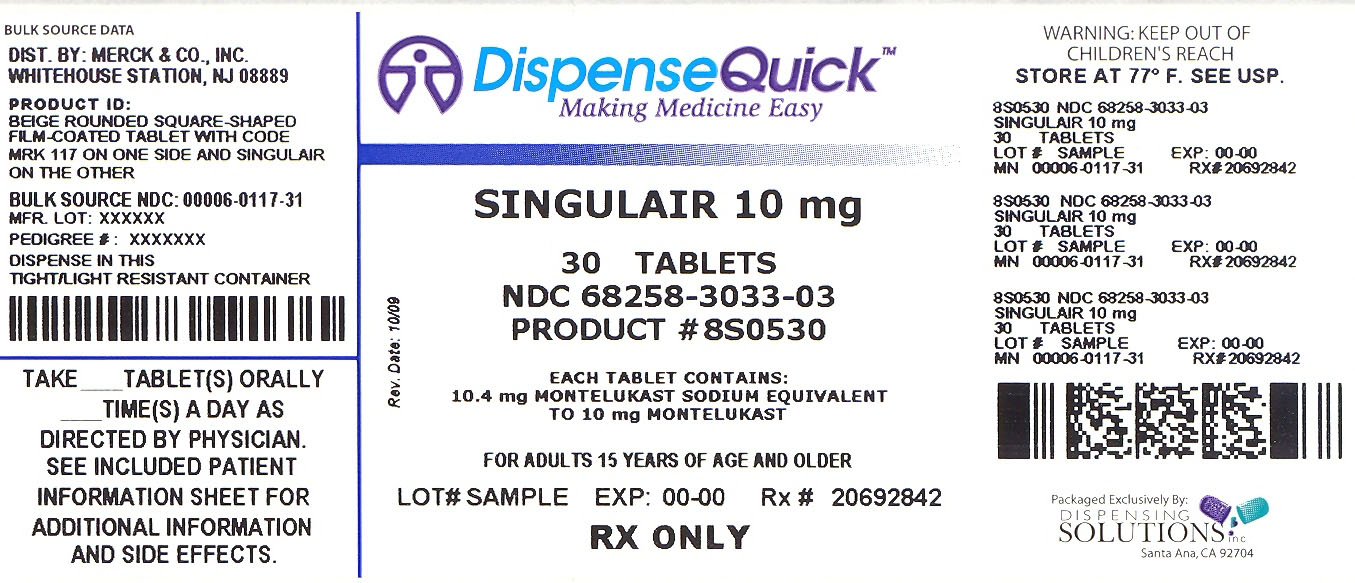 DRUG LABEL: SINGULAIR
NDC: 68258-3032 | Form: TABLET, CHEWABLE
Manufacturer: Dispensing Solutions Inc.
Category: prescription | Type: HUMAN PRESCRIPTION DRUG LABEL
Date: 20100301

ACTIVE INGREDIENTS: MONTELUKAST SODIUM 5 mg/1 1
INACTIVE INGREDIENTS: MANNITOL; CELLULOSE, MICROCRYSTALLINE; HYDROXYPROPYL CELLULOSE; FERRIC OXIDE RED; CROSCARMELLOSE SODIUM; ASPARTAME; MAGNESIUM STEARATE

SINGULAIR®
(MONTELUKAST SODIUM)
TABLETS, CHEWABLE TABLETS, AND ORAL GRANULES

DESCRIPTION

Montelukast sodium, the active ingredient in SINGULAIR [Registered trademark of MERCK & CO., Inc. COPYRIGHT © 1998-2009 MERCK & CO., Inc. All rights reserved] , is a selective and orally active leukotriene receptor antagonist that inhibits the cysteinyl leukotriene CysLT1 receptor.

Montelukast sodium is described chemically as [R -(E)]-1-[[[1-[3-[2-(7-chloro-2-quinolinyl)ethenyl]phenyl]-3-[2-(1-hydroxy-1-methylethyl)phenyl]propyl]thio]methyl]cyclopropaneacetic acid, monosodium salt.

The empirical formula is C35H35ClNNaO3S, and its molecular weight is 608.18. The structural formula is:

Montelukast sodium is a hygroscopic, optically active, white to off-white powder. Montelukast sodium is freely soluble in ethanol, methanol, and water and practically insoluble in acetonitrile.

Each 10-mg film-coated SINGULAIR tablet contains 10.4 mg montelukast sodium, which is equivalent to 10 mg of montelukast, and the following inactive ingredients: microcrystalline cellulose, lactose monohydrate, croscarmellose sodium, hydroxypropyl cellulose, and magnesium stearate. The film coating consists of: hydroxypropyl methylcellulose, hydroxypropyl cellulose, titanium dioxide, red ferric oxide, yellow ferric oxide, and carnauba wax.

Each 4-mg and 5-mg chewable SINGULAIR tablet contains 4.2 and 5.2 mg montelukast sodium, respectively, which are equivalent to 4 and 5 mg of montelukast, respectively. Both chewable tablets contain the following inactive ingredients: mannitol, microcrystalline cellulose, hydroxypropyl cellulose, red ferric oxide, croscarmellose sodium, cherry flavor, aspartame, and magnesium stearate.

Each packet of SINGULAIR 4-mg oral granules contains 4.2 mg montelukast sodium, which is equivalent to 4 mg of montelukast. The oral granule formulation contains the following inactive ingredients: mannitol, hydroxypropyl cellulose, and magnesium stearate.

CLINICAL PHARMACOLOGY

Mechanism of Action

The cysteinyl leukotrienes (LTC4, LTD4, LTE4) are products of arachidonic acid metabolism and are released from various cells, including mast cells and eosinophils. These eicosanoids bind to cysteinyl leukotriene (CysLT) receptors. The CysLT type-1 (CysLT1) receptor is found in the human airway (including airway smooth muscle cells and airway macrophages) and on other pro-inflammatory cells (including eosinophils and certain myeloid stem cells). CysLTs have been correlated with the pathophysiology of asthma and allergic rhinitis. In asthma, leukotriene-mediated effects include airway edema, smooth muscle contraction, and altered cellular activity associated with the inflammatory process. In allergic rhinitis, CysLTs are released from the nasal mucosa after allergen exposure during both early- and late-phase reactions and are associated with symptoms of allergic rhinitis. Intranasal challenge with CysLTs has been shown to increase nasal airway resistance and symptoms of nasal obstruction. SINGULAIR has not been assessed in intranasal challenge studies. The clinical relevance of intranasal challenge studies is unknown.

Montelukast is an orally active compound that binds with high affinity and selectivity to the CysLT1 receptor (in preference to other pharmacologically important airway receptors, such as the prostanoid, cholinergic, or β-adrenergic receptor). Montelukast inhibits physiologic actions of LTD4 at the CysLT1 receptor without any agonist activity.

Absorption

Montelukast is rapidly absorbed following oral administration. After administration of the 10-mg film-coated tablet to fasted adults, the mean peak montelukast plasma concentration (Cmax) is achieved in 3 to 4 hours (Tmax). The mean oral bioavailability is 64%. The oral bioavailability and Cmax are not influenced by a standard meal in the morning.

For the 5-mg chewable tablet, the mean Cmax is achieved in 2 to 2.5 hours after administration to adults in the fasted state. The mean oral bioavailability is 73% in the fasted state versus 63% when administered with a standard meal in the morning.

For the 4-mg chewable tablet, the mean Cmax is achieved 2 hours after administration in pediatric patients 2 to 5 years of age in the fasted state.

The 4-mg oral granule formulation is bioequivalent to the 4-mg chewable tablet when administered to adults in the fasted state. The co-administration of the oral granule formulation with applesauce did not have a clinically significant effect on the pharmacokinetics of montelukast. A high fat meal in the morning did not affect the AUC of montelukast oral granules; however, the meal decreased Cmax by 35% and prolonged Tmax from 2.3 ± 1.0 hours to 6.4 ± 2.9 hours.

The safety and efficacy of SINGULAIR in patients with asthma were demonstrated in clinical trials in which the 10-mg film-coated tablet and 5-mg chewable tablet formulations were administered in the evening without regard to the time of food ingestion. The safety of SINGULAIR in patients with asthma was also demonstrated in clinical trials in which the 4-mg chewable tablet and 4-mg oral granule formulations were administered in the evening without regard to the time of food ingestion. The safety and efficacy of SINGULAIR in patients with seasonal allergic rhinitis were demonstrated in clinical trials in which the 10-mg film-coated tablet was administered in the morning or evening without regard to the time of food ingestion.

The comparative pharmacokinetics of montelukast when administered as two 5-mg chewable tablets versus one 10-mg film-coated tablet have not been evaluated.

Distribution

Montelukast is more than 99% bound to plasma proteins. The steady state volume of distribution of montelukast averages 8 to 11 liters. Studies in rats with radiolabeled montelukast indicate minimal distribution across the blood-brain barrier. In addition, concentrations of radiolabeled material at 24 hours postdose were minimal in all other tissues.

Metabolism

Montelukast is extensively metabolized. In studies with therapeutic doses, plasma concentrations of metabolites of montelukast are undetectable at steady state in adults and pediatric patients.

In vitro studies using human liver microsomes indicate that cytochromes P450 3A4 and 2C9 are involved in the metabolism of montelukast. Clinical studies investigating the effect of known inhibitors of cytochromes P450 3A4 (e.g., ketoconazole, erythromycin) or 2C9 (e.g., fluconazole) on montelukast pharmacokinetics have not been conducted. Based on further in vitro results in human liver microsomes, therapeutic plasma concentrations of montelukast do not inhibit cytochromes P450 3A4, 2C9, 1A2, 2A6, 2C19, or 2D6 (see Drug Interactions). In vitro studies have shown that montelukast is a potent inhibitor of cytochrome P450 2C8; however, data from a clinical drug-drug interaction study involving montelukast and rosiglitazone (a probe substrate representative of drugs primarily metabolized by CYP2C8) demonstrated that montelukast does not inhibit CYP2C8 in vivo, and therefore is not anticipated to alter the metabolism of drugs metabolized by this enzyme (see Drug Interactions).

Elimination

The plasma clearance of montelukast averages 45 mL/min in healthy adults. Following an oral dose of radiolabeled montelukast, 86% of the radioactivity was recovered in 5-day fecal collections and <0.2% was recovered in urine. Coupled with estimates of montelukast oral bioavailability, this indicates that montelukast and its metabolites are excreted almost exclusively via the bile.

In several studies, the mean plasma half-life of montelukast ranged from 2.7 to 5.5 hours in healthy young adults. The pharmacokinetics of montelukast are nearly linear for oral doses up to 50 mg. During once-daily dosing with 10-mg montelukast, there is little accumulation of the parent drug in plasma (14%).

Gender

The pharmacokinetics of montelukast are similar in males and females.

Elderly

The pharmacokinetic profile and the oral bioavailability of a single 10-mg oral dose of montelukast are similar in elderly and younger adults. The plasma half-life of montelukast is slightly longer in the elderly. No dosage adjustment in the elderly is required.

Race

Pharmacokinetic differences due to race have not been studied.

Hepatic Insufficiency

Patients with mild-to-moderate hepatic insufficiency and clinical evidence of cirrhosis had evidence of decreased metabolism of montelukast resulting in 41% (90% CI=7%, 85%) higher mean montelukast area under the plasma concentration curve (AUC) following a single 10-mg dose. The elimination of montelukast was slightly prolonged compared with that in healthy subjects (mean half-life, 7.4 hours). No dosage adjustment is required in patients with mild-to-moderate hepatic insufficiency. The pharmacokinetics of SINGULAIR in patients with more severe hepatic impairment or with hepatitis have not been evaluated.

Renal Insufficiency

Since montelukast and its metabolites are not excreted in the urine, the pharmacokinetics of montelukast were not evaluated in patients with renal insufficiency. No dosage adjustment is recommended in these patients.

Adolescents and Pediatric Patients

Pharmacokinetic studies evaluated the systemic exposure of the 4-mg oral granule formulation in pediatric patients 6 to 23 months of age, the 4-mg chewable tablets in pediatric patients 2 to 5 years of age, the 5-mg chewable tablets in pediatric patients 6 to 14 years of age, and the 10-mg film-coated tablets in young adults and adolescents ≥15 years of age.

The plasma concentration profile of montelukast following administration of the 10-mg film-coated tablet is similar in adolescents ≥15 years of age and young adults. The 10-mg film-coated tablet is recommended for use in patients ≥15 years of age.

The mean systemic exposure of the 4-mg chewable tablet in pediatric patients 2 to 5 years of age and the 5-mg chewable tablets in pediatric patients 6 to 14 years of age is similar to the mean systemic exposure of the 10-mg film-coated tablet in adults. The 5-mg chewable tablet should be used in pediatric patients 6 to 14 years of age and the 4-mg chewable tablet should be used in pediatric patients 2 to 5 years of age.

In children 6 to 11 months of age, the systemic exposure to montelukast and the variability of plasma montelukast concentrations were higher than those observed in adults. Based on population analyses, the mean AUC (4296 ng•hr/mL [range 1200 to 7153]) was 60% higher and the mean Cmax (667 ng/mL [range 201 to 1058]) was 89% higher than those observed in adults (mean AUC 2689 ng•hr/mL [range 1521 to 4595]) and mean Cmax (353 ng/mL [range 180 to 548]). The systemic exposure in children 12 to 23 months of age was less variable, but was still higher than that observed in adults. The mean AUC (3574 ng•hr/mL [range 2229 to 5408]) was 33% higher and the mean Cmax (562 ng/mL [range 296 to 814]) was 60% higher than those observed in adults. Safety and tolerability of montelukast in a single-dose pharmacokinetic study in 26 children 6 to 23 months of age were similar to that of patients two years and above (see ADVERSE REACTIONS). The 4-mg oral granule formulation should be used for pediatric patients 12 to 23 months of age for the treatment of asthma, or for pediatric patients 6 to 23 months of age for the treatment of perennial allergic rhinitis. Since the 4-mg oral granule formulation is bioequivalent to the 4-mg chewable tablet, it can also be used as an alternative formulation to the 4-mg chewable tablet in pediatric patients 2 to 5 years of age.

Drug Interactions

Montelukast at a dose of 10 mg once daily dosed to pharmacokinetic steady state:

- did not cause clinically significant changes in the kinetics of a single intravenous dose of theophylline (predominantly a cytochrome P450 1A2 substrate).
- did not change the pharmacokinetic profile of warfarin (primarily a substrate of CYP 2C9, 3A4 and 1A2) or influence the effect of a single 30-mg oral dose of warfarin on prothrombin time or the INR (International Normalized Ratio).
- did not change the pharmacokinetic profile or urinary excretion of immunoreactive digoxin.
- did not change the plasma concentration profile of terfenadine (a substrate of CYP 3A4) or fexofenadine, its carboxylated metabolite, and did not prolong the QTc interval following co-administration with terfenadine 60 mg twice daily.

Montelukast at doses of ≥100 mg daily dosed to pharmacokinetic steady state:

- did not significantly alter the plasma concentrations of either component of an oral contraceptive containing norethindrone 1 mg/ethinyl estradiol 35 mcg.
- did not cause any clinically significant change in plasma profiles of prednisone or prednisolone following administration of either oral prednisone or intravenous prednisolone.

Phenobarbital, which induces hepatic metabolism, decreased the AUC of montelukast approximately 40% following a single 10-mg dose of montelukast. No dosage adjustment for SINGULAIR is recommended. It is reasonable to employ appropriate clinical monitoring when potent cytochrome P450 enzyme inducers, such as phenobarbital or rifampin, are co-administered with SINGULAIR.

Montelukast is a potent inhibitor of P450 2C8 in vitro. However, data from a clinical drug-drug interaction study involving montelukast and rosiglitazone (a probe substrate representative of drugs primarily metabolized by CYP2C8) in 12 healthy individuals demonstrated that the pharmacokinetics of rosiglitazone are not altered when the drugs are coadministered, indicating that montelukast does not inhibit CYP2C8 in vivo . Therefore, montelukast is not anticipated to alter the metabolism of drugs metabolized by this enzyme (e.g., paclitaxel, rosiglitazone, and repaglinide.)

Pharmacodynamics

Montelukast causes inhibition of airway cysteinyl leukotriene receptors as demonstrated by the ability to inhibit bronchoconstriction due to inhaled LTD4 in asthmatics. Doses as low as 5 mg cause substantial blockage of LTD4-induced bronchoconstriction. In a placebo-controlled, crossover study (n=12), SINGULAIR inhibited early- and late-phase bronchoconstriction due to antigen challenge by 75% and 57%, respectively.

The effect of SINGULAIR on eosinophils in the peripheral blood was examined in clinical trials. In patients with asthma aged 2 years and older who received SINGULAIR, a decrease in mean peripheral blood eosinophil counts ranging from 9% to 15% was noted, compared with placebo, over the double-blind treatment periods. In patients with seasonal allergic rhinitis aged 15 years and older who received SINGULAIR, a mean increase of 0.2% in peripheral blood eosinophil counts was noted, compared with a mean increase of 12.5% in placebo-treated patients, over the double-blind treatment periods; this reflects a mean difference of 12.3% in favor of SINGULAIR. The relationship between these observations and the clinical benefits of montelukast noted in the clinical trials is not known (see CLINICAL PHARMACOLOGY, Clinical Studies).

GENERAL

There have been no clinical trials in asthmatics to evaluate the relative efficacy of morning versus evening dosing. The pharmacokinetics of montelukast are similar whether dosed in the morning or evening. Efficacy has been demonstrated for asthma when montelukast was administered in the evening without regard to time of food ingestion. Efficacy was demonstrated for seasonal allergic rhinitis when montelukast was administered in the morning or the evening without regard to time of food ingestion.

ADULTS AND ADOLESCENTS 15 YEARS OF AGE AND OLDER

Clinical trials in adults and adolescents 15 years of age and older demonstrated there is no additional clinical benefit to montelukast doses above 10 mg once daily. This was shown in two chronic asthma trials using doses up to 200 mg once daily and in one exercise challenge study using doses up to 50 mg, evaluated at the end of the once-daily dosing interval.

The efficacy of SINGULAIR for the chronic treatment of asthma in adults and adolescents 15 years of age and older was demonstrated in two (U.S. and Multinational) similarly designed, randomized, 12-week, double-blind, placebo-controlled trials in 1576 patients (795 treated with SINGULAIR, 530 treated with placebo, and 251 treated with active control). The patients studied were mild and moderate, non-smoking asthmatics who required approximately 5 puffs of inhaled β-agonist per day on an “as-needed” basis. The patients had a mean baseline percent of predicted forced expiratory volume in 1 second (FEV1) of 66% (approximate range, 40 to 90%). The co-primary endpoints in these trials were FEV1 and daytime asthma symptoms. Secondary endpoints included morning and evening peak expiratory flow rates (AM PEFR, PM PEFR), rescue β-agonist requirements, nocturnal awakening due to asthma, and other asthma-related outcomes. In both studies after 12 weeks, a random subset of patients receiving SINGULAIR was switched to placebo for an additional 3 weeks of double-blind treatment to evaluate for possible rebound effects. The results of the U.S. trial on the primary endpoint, FEV1, expressed as mean percent change from baseline, are shown in FIGURE 1.

FIGURE 1: FEV1 Mean Percent Change from Baseline (U.S. Trial)

The effect of SINGULAIR on other primary and secondary endpoints is shown in TABLE 1 as combined analyses of the U.S. and Multinational trials.

TABLE 1: Effect of SINGULAIR on Primary and Secondary Endpoints in Placebo-controlled Trials (Combined Analyses - U.S. and Multinational Trials)
 | SINGULAIR |  | Placebo
Endpoint | Baseline | Mean Change from Baseline | Baseline | Mean Change from Baseline
Daytime Asthma Symptoms (0 to 6 scale) | 2.43 | -0.45 [p<0.001, compared with placebo] | 2.45 | -0.22
β-agonist (puffs per day) | 5.38 | -1.56 | 5.55 | -0.41
AM PEFR (L/min) | 361.3 | 24.5 | 364.9 | 3.3
PM PEFR (L/min) | 385.2 | 17.9 | 389.3 | 2.0
Nocturnal Awakenings (#/week) | 5.37 | -1.84 | 5.44 | -0.79

In adult patients, SINGULAIR reduced “as-needed” β-agonist use by 26.1% from baseline compared with 4.6% for placebo. In patients with nocturnal awakenings of at least 2 nights per week, SINGULAIR reduced the nocturnal awakenings by 34% from baseline, compared with 15% for placebo (combined analysis).

SINGULAIR, compared with placebo, significantly improved other protocol-defined, asthma-related outcome measurements (see TABLE 2).

TABLE 2: Effect of SINGULAIR on Asthma-Related Outcome Measurements (Combined Analyses - U.S. and Multinational Trials)
 | SINGULAIR | Placebo
Asthma Attack [Asthma Attack defined as utilization of health-care resources such as an unscheduled visit to a doctor's office, emergency room, or hospital; or treatment with oral, intravenous, or intramuscular corticosteroid.] (% of patients) | 11.6 [p<0.001, compared with placebo] | 18.4
Oral Corticosteroid Rescue (% of patients) | 10.7 | 17.5
Discontinuation Due to Asthma (% of patients) | 1.4 [p<0.01, compared with placebo] | 4.0
Asthma Exacerbations [Asthma Exacerbation defined by specific clinically important decreases in PEFR, increase in β-agonist use, increases in day or nighttime symptoms, or the occurrence of an asthma attack.] (% of days) | 12.8 | 20.5
Asthma Control Days [An Asthma Control Day defined as a day without any of the following: nocturnal awakening, use of more than 2 puffs of β-agonist, or an asthma attack.] (% of days) | 38.5 | 27.2
Physicians’ Global Evaluation (score) [Physicians’ evaluation of the patient’s asthma, ranging from 0 to 6 (“very much better” through “very much worse”, respectively).] | 1.77 | 2.43
Patients’ Global Evaluation (score) [Patients’ evaluation of asthma, ranging from 0 to 6 (“very much better” through “very much worse”, respectively).] | 1.60 | 2.15

In one of these trials, a non-U.S. formulation of inhaled beclomethasone dipropionate dosed at 200 mcg (two puffs of 100 mcg ex-valve) twice daily with a spacer device was included as an active control. Over the 12-week treatment period, the mean percentage change in FEV1 over baseline for SINGULAIR and beclomethasone were 7.49% vs 13.3% (p<0.001) respectively, see FIGURE 2; and the change in daytime symptom scores was -0.49 vs -0.70 on a 0 to 6 scale (p<0.001) for SINGULAIR and beclomethasone, respectively. The percentages of individual patients treated with SINGULAIR or beclomethasone achieving any given percentage change in FEV1 from baseline are shown in FIGURE 3.

FIGURE 2: FEV1 Mean Percent Change From Baseline (Multinational Trial)
FIGURE 3: FEV1 Distribution of Indvidual Patient Response (Multinational Trial)

Onset of Action and Maintenance of Benefits

In each placebo-controlled trial in adults, the treatment effect of SINGULAIR, measured by daily diary card parameters, including symptom scores, “as-needed” β-agonist use, and PEFR measurements, was achieved after the first dose and was maintained throughout the dosing interval (24 hours). No significant change in treatment effect was observed during continuous once-daily evening administration in non-placebo-controlled extension trials for up to one year. Withdrawal of SINGULAIR in asthmatic patients after 12 weeks of continuous use did not cause rebound worsening of asthma.

PEDIATRIC PATIENTS 6 TO 14 YEARS OF AGE

The efficacy of SINGULAIR in pediatric patients 6 to 14 years of age was demonstrated in one 8-week, double-blind, placebo-controlled trial in 336 patients (201 treated with SINGULAIR and 135 treated with placebo) using an inhaled β-agonist on an “as-needed” basis. The patients had a mean baseline percent predicted FEV1 of 72% (approximate range, 45 to 90%) and a mean daily inhaled β-agonist requirement of 3.4 puffs of albuterol. Approximately 36% of the patients were on inhaled corticosteroids.

Compared with placebo, treatment with one 5-mg SINGULAIR chewable tablet daily resulted in a significant improvement in mean morning FEV1 percent change from baseline (8.7% in the group treated with SINGULAIR vs 4.2% change from baseline in the placebo group, p<0.001). There was a significant decrease in the mean percentage change in daily “as-needed” inhaled β-agonist use (11.7% decrease from baseline in the group treated with SINGULAIR vs 8.2% increase from baseline in the placebo group, p<0.05). This effect represents a mean decrease from baseline of 0.56 and 0.23 puffs per day for the montelukast and placebo groups, respectively. Subgroup analyses indicated that younger pediatric patients aged 6 to 11 had efficacy results comparable to those of the older pediatric patients aged 12 to 14.

SINGULAIR, one 5-mg chewable tablet daily at bedtime, significantly decreased the percent of days asthma exacerbations occurred (SINGULAIR 20.6% vs placebo 25.7%, p≤0.05). (See TABLE 2 for definition of asthma exacerbation.) Parents’ global asthma evaluations (parental evaluations of the patients’ asthma, see TABLE 2 for definition of score) were significantly better with SINGULAIR compared with placebo (SINGULAIR 1.34 vs placebo 1.69, p≤0.05).

Similar to the adult studies, no significant change in the treatment effect was observed during continuous once-daily administration in one open-label extension trial without a concurrent placebo group for up to 6 months.

PEDIATRIC PATIENTS 2 TO 5 YEARS OF AGE

The efficacy of SINGULAIR for the chronic treatment of asthma in pediatric patients 2 to 5 years of age was explored in a 12-week, placebo-controlled safety and tolerability study in 689 patients, 461 of whom were treated with SINGULAIR. While the primary objective was to determine the safety and tolerability of SINGULAIR in this age group, the study included exploratory efficacy evaluations, including daytime and overnight asthma symptom scores, β-agonist use, oral corticosteroid rescue, and the physician’s global evaluation. The findings of these exploratory efficacy evaluations, along with pharmacokinetics and extrapolation of efficacy data from older patients, support the overall conclusion that SINGULAIR is efficacious in the maintenance treatment of asthma in patients 2 to 5 years of age.

EFFECTS IN PATIENTS ON CONCOMITANT INHALED CORTICOSTEROIDS

Separate trials in adults evaluated the ability of SINGULAIR to add to the clinical effect of inhaled corticosteroids and to allow inhaled corticosteroid tapering when used concomitantly.

One randomized, placebo-controlled, parallel-group trial (n=226) enrolled stable asthmatic adults with a mean FEV1 of approximately 84% of predicted who were previously maintained on various inhaled corticosteroids (delivered by metered-dose aerosol or dry powder inhalers). The types of inhaled corticosteroids and their mean baseline requirements included beclomethasone dipropionate (mean dose, 1203 mcg/day), triamcinolone acetonide (mean dose, 2004 mcg/day), flunisolide (mean dose, 1971 mcg/day), fluticasone propionate (mean dose, 1083 mcg/day), or budesonide (mean dose, 1192 mcg/day). Some of these inhaled corticosteroids were non-U.S.-approved formulations, and doses expressed may not be ex-actuator. The pre-study inhaled corticosteroid requirements were reduced by approximately 37% during a 5- to 7-week placebo run-in period designed to titrate patients toward their lowest effective inhaled corticosteroid dose. Treatment with SINGULAIR resulted in a further 47% reduction in mean inhaled corticosteroid dose compared with a mean reduction of 30% in the placebo group over the 12-week active treatment period (p≤0.05). Approximately 40% of the montelukast-treated patients and 29% of the placebo-treated patients could be tapered off inhaled corticosteroids and remained off inhaled corticosteroids at the conclusion of the study (p=NS). It is not known whether the results of this study can be generalized to asthmatics who require higher doses of inhaled corticosteroids or systemic corticosteroids.

In another randomized, placebo-controlled, parallel-group trial (n=642) in a similar population of adult patients previously maintained, but not adequately controlled, on inhaled corticosteroids (beclomethasone 336 mcg/day), the addition of SINGULAIR to beclomethasone resulted in statistically significant improvements in FEV1 compared with those patients who were continued on beclomethasone alone or those patients who were withdrawn from beclomethasone and treated with montelukast or placebo alone over the last 10 weeks of the 16-week, blinded treatment period. Patients who were randomized to treatment arms containing beclomethasone had statistically significantly better asthma control than those patients randomized to SINGULAIR alone or placebo alone as indicated by FEV1, daytime asthma symptoms, PEFR, nocturnal awakenings due to asthma, and “as-needed” β-agonist requirements.

In adult asthmatic patients with documented aspirin sensitivity, nearly all of whom were receiving concomitant inhaled and/or oral corticosteroids, a 4-week, randomized, parallel-group trial (n=80) demonstrated that SINGULAIR, compared with placebo, resulted in significant improvement in parameters of asthma control. The magnitude of effect of SINGULAIR in aspirin-sensitive patients was similar to the effect observed in the general population of asthmatic patients studied. The effect of SINGULAIR on the bronchoconstrictor response to aspirin or other non-steroidal anti-inflammatory drugs in aspirin-sensitive asthmatic patients has not been evaluated (see PRECAUTIONS, General).

SINGLE-DOSE ADMINISTRATION (ADULTS AND ADOLESCENTS)

The efficacy of SINGULAIR, 10 mg, when given as a single dose 2 hours before exercise for the prevention of exercise-induced bronchoconstriction (EIB) was investigated in three (U.S. and Multinational), randomized, double-blind, placebo-controlled crossover studies that included a total of 160 adult and adolescent patients 15 years of age and older with exercise-induced bronchoconstriction. Exercise challenge testing was conducted at 2 hours, 8.5 or 12 hours, and 24 hours following administration of a single dose of study drug (SINGULAIR 10 mg or placebo). The primary endpoint was the mean maximum percent fall in FEV1 following the 2 hours post-dose exercise challenge in all three studies (Study A, Study B, and Study C). In Study A, a single dose of SINGULAIR 10 mg demonstrated a statistically significant protective benefit against EIB when taken 2 hours prior to exercise. Some patients were protected from exercise-induced bronchoconstriction at 8.5 and 24 hours after administration; however, some patients were not. The results for the mean maximum percent fall at each timepoint in Study A are shown in the TABLE 3 below and are representative of the results from the other two studies.

TABLE 3: Mean Maximum Percent Fall in FEV1 Following Exercise Challenge in Study A (N=47)
Time of exercise challenge following medication administration | Mean Maximum percent fall in FEV1 [Least squares-mean] |  | Treatment difference % for SINGULAIR versus Placebo (95%CI)
 | SINGULAIR | Placebo
2 hours | 13 | 22 | -9 (-12, -5)
8.5 hours | 12 | 17 | -5 (-9, -2)
24 hours | 10 | 14 | -4 (-7, -1)

CHRONIC ADMINISTRATION (ADULTS AND PEDIATRIC PATIENTS)

In a 12-week, randomized, double-blind, parallel group study of 110 adult and adolescent asthmatics 15 years of age and older, with a mean baseline FEV1 percent of predicted of 83% and with documented exercise-induced exacerbation of asthma, treatment with SINGULAIR, 10 mg, once daily in the evening, resulted in a statistically significant reduction in mean maximal percent fall in FEV1 and mean time to recovery to within 5% of the pre-exercise FEV1. Exercise challenge was conducted at the end of the dosing interval (i.e., 20 to 24 hours after the preceding dose). This effect was maintained throughout the 12-week treatment period indicating that tolerance did not occur. SINGULAIR did not, however, prevent clinically significant deterioration in maximal percent fall in FEV1 after exercise (i.e., ≥20% decrease from pre-exercise baseline) in 52% of patients studied. In a separate crossover study in adults, a similar effect was observed after two once-daily 10-mg doses of SINGULAIR.

In pediatric patients 6 to 14 years of age, using the 5-mg chewable tablet, a 2-day crossover study demonstrated effects similar to those observed in adults when exercise challenge was conducted at the end of the dosing interval (i.e., 20 to 24 hours after the preceding dose).

Daily administration of SINGULAIR for the chronic treatment of asthma has not been established to prevent acute episodes of exercise-induced bronchoconstriction.

Clinical Studies – Growth Rate in Pediatric Patients

A 56-week, multi-center, double-blind, randomized, active- and placebo-controlled parallel group study was conducted to assess the effect of SINGULAIR on growth rate in 360 patients with mild asthma, aged 6 to 8 years. Treatment groups included SINGULAIR 5 mg once daily, placebo, and beclomethasone dipropionate administered as 168 mcg twice daily with a spacer device. For each subject, a growth rate was defined as the slope of a linear regression line fit to the height measurements over 56 weeks. The primary comparison was the difference in growth rates between SINGULAIR and placebo groups. Growth rates, expressed as least-squares (LS) mean (95% CI) in cm/year, for the SINGULAIR, placebo, and beclomethasone treatment groups were 5.67 (5.46, 5.88), 5.64 (5.42, 5.86), and 4.86 (4.64, 5.08), respectively. The differences in growth rates, expressed as least squares (LS) mean (95% CI) in cm/year, for SINGULAIR minus placebo, beclomethasone minus placebo, and SINGULAIR minus beclomethasone treatment groups were 0.03 (-0.26, 0.31), -0.78 (-1.06, -0.49); and 0.81 (0.53, 1.09), respectively. Growth rate (expressed as mean change in height over time) for each treatment group is shown in Figure 4.

FIGURE 4: Change in Height (cm) from Randomization Visit by Scheduled Week (Treatment Group Mean ± Standard Error* of the Mean)

Clinical Studies – Seasonal Allergic Rhinitis

The efficacy of SINGULAIR tablets for the treatment of seasonal allergic rhinitis was investigated in 5 similarly designed, randomized, double-blind, parallel-group, placebo- and active-controlled (loratadine) trials conducted in North America. The 5 trials enrolled a total of 5029 patients, of whom 1799 were treated with SINGULAIR tablets. Patients were 15 to 82 years of age with a history of seasonal allergic rhinitis, a positive skin test to at least one relevant seasonal allergen, and active symptoms of seasonal allergic rhinitis at study entry.

The period of randomized treatment was 2 weeks in 4 trials and 4 weeks in one trial. The primary outcome variable was mean change from baseline in daytime nasal symptoms score (the average of individual scores of nasal congestion, rhinorrhea, nasal itching, sneezing) as assessed by patients on a 0-3 categorical scale.

Four of the five trials showed a significant reduction in daytime nasal symptoms scores with SINGULAIR 10-mg tablets compared with placebo. The efficacy results of one trial are shown below; the remaining three trials that demonstrated efficacy showed similar results. The mean changes from baseline in daytime nasal symptoms score in the treatment groups that received SINGULAIR tablets, loratadine and placebo are shown in TABLE 4.

TABLE 4: Effects of SINGULAIR on Daytime Nasal Symptoms Score [Average of individual scores of nasal congestion, rhinorrhea, nasal itching, sneezing as assessed by patients on a 0-3 categorical scale.] in a Placebo- and Active-controlled Trial in Patients with Seasonal Allergic Rhinitis
Treatment Group (N) | Baseline Mean Score | Mean Change from Baseline | Difference Between Treatment and Placebo (95% CI) Least-Squares Mean
SINGULAIR 10 mg (344) | 2.09 | -0.39 | -0.13 [Statistically different from placebo (p≤0.001).] (-0.21, -0.06)
Placebo (351) | 2.10 | -0.26 | N.A.
Active Control [The study was not designed for statistical comparison between SINGULAIR and the active control (loratadine).] (Loratadine 10 mg) (599) | 2.06 | -0.46 | -0.24 (-0.31, -0.17)

Clinical Studies – Perennial Allergic Rhinitis

The efficacy of SINGULAIR tablets for the treatment of perennial allergic rhinitis was investigated in 2 randomized, double-blind, placebo-controlled studies conducted in North America and Europe. The two studies enrolled a total of 3357 patients, of whom 1632 received SINGULAIR 10-mg tablets. Patients 15 to 82 years of age with perennial allergic rhinitis as confirmed by history and a positive skin test to at least one relevant perennial allergen (dust mites, animal dander, and/or mold spores), who had active symptoms at the time of study entry, were enrolled.

In the study in which efficacy was demonstrated, SINGULAIR 10-mg tablets once daily was shown to significantly reduce symptoms of perennial allergic rhinitis over a 6-week treatment period (TABLE 5); in this study the primary outcome variable was mean change from baseline in daytime nasal symptoms score (the average of individual scores of nasal congestion, rhinorrhea, and sneezing).

TABLE 5: Effects of SINGULAIR on Daytime Nasal Symptoms Score [Average of individual scores of nasal congestion, rhinorrhea, sneezing as assessed by patients on a 0-3 categorical scale.] in a Placebo-controlled Trial in Patients with Perennial Allergic Rhinitis
Treatment Group (N) | Baseline Mean Score | Mean Change from Baseline | Difference Between Treatment and Placebo (95% CI) Least-Squares Mean
SINGULAIR 10 mg (1000) | 2.09 | -0.42 | -0.08 [Statistically different from placebo (p≤0.001).] (-0.12, -0.04)
Placebo (980) | 2.10 | -0.35 | N.A.

The other 6-week study evaluated SINGULAIR 10 mg (n=626), placebo (n=609), and an active-control (cetirizine 10 mg; n=120). The primary analysis compared the mean change from baseline in daytime nasal symptoms score for SINGULAIR vs. placebo over the first 4 weeks of treatment; the study was not designed for statistical comparison between SINGULAIR and the active-control. The primary outcome variable included nasal itching in addition to nasal congestion, rhinorrhea, and sneezing. The estimated difference between SINGULAIR and placebo was -0.04 with a 95% CI of (-0.09, 0.01). The estimated difference between the active-control and placebo was -0.10 with a 95% CI of (-0.19, -0.01).

INDICATIONS AND USAGE

SINGULAIR is indicated for the prophylaxis and chronic treatment of asthma in adults and pediatric patients 12 months of age and older.

SINGULAIR is indicated for prevention of exercise-induced bronchoconstriction in patients 15 years of age and older.

SINGULAIR is indicated for the relief of symptoms of allergic rhinitis (seasonal allergic rhinitis in adults and pediatric patients 2 years of age and older, and perennial allergic rhinitis in adults and pediatric patients 6 months of age and older).

CONTRAINDICATIONS

Hypersensitivity to any component of this product.

PRECAUTIONS

General

SINGULAIR is not indicated for use in the reversal of bronchospasm in acute asthma attacks, including status asthmaticus.

Patients should be advised to have appropriate rescue medication available. Therapy with SINGULAIR can be continued during acute exacerbations of asthma. Patients who have exacerbations of asthma after exercise should have available for rescue a short-acting inhaled β-agonist.

While the dose of inhaled corticosteroid may be reduced gradually under medical supervision, SINGULAIR should not be abruptly substituted for inhaled or oral corticosteroids.

Patients with known aspirin sensitivity should continue avoidance of aspirin or non-steroidal anti-inflammatory agents while taking SINGULAIR. Although SINGULAIR is effective in improving airway function in asthmatics with documented aspirin sensitivity, it has not been shown to truncate bronchoconstrictor response to aspirin and other non-steroidal anti-inflammatory drugs in aspirin-sensitive asthmatic patients (see CLINICAL PHARMACOLOGY, Clinical Studies).

Neuropsychiatric Events

Neuropsychiatric events have been reported in adult, adolescent, and pediatric patients taking SINGULAIR. Post-marketing reports with SINGULAIR use include agitation, aggressive behavior or hostility, anxiousness, depression, dream abnormalities, hallucinations, insomnia, irritability, restlessness, somnambulism, suicidal thinking and behavior (including suicide), and tremor. The clinical details of some post-marketing reports involving SINGULAIR appear consistent with a drug-induced effect.

Patients and prescribers should be alert for neuropsychiatric events. Patients should be instructed to notify their prescriber if these changes occur. Prescribers should carefully evaluate the risks and benefits of continuing treatment with SINGULAIR if such events occur (see ADVERSE REACTIONS, Post-Marketing Experience).

Eosinophilic Conditions

In rare cases, patients with asthma on therapy with SINGULAIR may present with systemic eosinophilia, sometimes presenting with clinical features of vasculitis consistent with Churg-Strauss syndrome, a condition which is often treated with systemic corticosteroid therapy. These events usually, but not always, have been associated with the reduction of oral corticosteroid therapy. Physicians should be alert to eosinophilia, vasculitic rash, worsening pulmonary symptoms, cardiac complications, and/or neuropathy presenting in their patients. A causal association between SINGULAIR and these underlying conditions has not been established (see ADVERSE REACTIONS).

Information for Patients

- Patients should be advised to take SINGULAIR daily as prescribed, even when they are asymptomatic, as well as during periods of worsening asthma, and to contact their physicians if their asthma is not well controlled.
- Patients should be advised that oral SINGULAIR is not for the treatment of acute asthma attacks. They should have appropriate short-acting inhaled β-agonist medication available to treat asthma exacerbations. Patients who have exacerbations of asthma after exercise should be instructed to have available for rescue a short-acting inhaled β-agonist. Daily administration of SINGULAIR for the chronic treatment of asthma has not been established to prevent acute episodes of exercise-induced bronchoconstriction.
- Patients should be advised that, while using SINGULAIR, medical attention should be sought if short-acting inhaled bronchodilators are needed more often than usual, or if more than the maximum number of inhalations of short-acting bronchodilator treatment prescribed for a 24-hour period are needed.
- Patients receiving SINGULAIR should be instructed not to decrease the dose or stop taking any other anti-asthma medications unless instructed by a physician.
- Patients should be instructed to notify their physician if neuropsychiatric events occur while using SINGULAIR.
- Patients with known aspirin sensitivity should be advised to continue avoidance of aspirin or non-steroidal anti-inflammatory agents while taking SINGULAIR.

Chewable Tablets

- Phenylketonurics: Phenylketonuric patients should be informed that the 4-mg and 5-mg chewable tablets contain phenylalanine (a component of aspartame), 0.674 and 0.842 mg per 4-mg and 5-mg chewable tablet, respectively.

Drug Interactions

SINGULAIR has been administered with other therapies routinely used in the prophylaxis and chronic treatment of asthma with no apparent increase in adverse reactions. In drug-interaction studies, the recommended clinical dose of montelukast did not have clinically important effects on the pharmacokinetics of the following drugs: theophylline, prednisone, prednisolone, oral contraceptives (norethindrone 1 mg/ethinyl estradiol 35 mcg), terfenadine, digoxin, and warfarin.

Although additional specific interaction studies were not performed, SINGULAIR was used concomitantly with a wide range of commonly prescribed drugs in clinical studies without evidence of clinical adverse interactions. These medications included thyroid hormones, sedative hypnotics, non-steroidal anti-inflammatory agents, benzodiazepines, and decongestants.

Phenobarbital, which induces hepatic metabolism, decreased the AUC of montelukast approximately 40% following a single 10-mg dose of montelukast. No dosage adjustment for SINGULAIR is recommended. It is reasonable to employ appropriate clinical monitoring when potent cytochrome P450 enzyme inducers, such as phenobarbital or rifampin, are co-administered with SINGULAIR.

Carcinogenesis, Mutagenesis, Impairment of Fertility

No evidence of tumorigenicity was seen in carcinogenicity studies of either 2 years in Sprague-Dawley rats or 92 weeks in mice at oral gavage doses up to 200 mg/kg/day or 100 mg/kg/day, respectively. The estimated exposure in rats was approximately 120 and 75 times the area under the plasma concentration versus time curve (AUC) for adults and children, respectively, at the maximum recommended daily oral dose. The estimated exposure in mice was approximately 45 and 25 times the AUC for adults and children, respectively, at the maximum recommended daily oral dose.

Montelukast demonstrated no evidence of mutagenic or clastogenic activity in the following assays: the microbial mutagenesis assay, the V-79 mammalian cell mutagenesis assay, the alkaline elution assay in rat hepatocytes, the chromosomal aberration assay in Chinese hamster ovary cells, and in the in vivo mouse bone marrow chromosomal aberration assay.

In fertility studies in female rats, montelukast produced reductions in fertility and fecundity indices at an oral dose of 200 mg/kg (estimated exposure was approximately 70 times the AUC for adults at the maximum recommended daily oral dose). No effects on female fertility or fecundity were observed at an oral dose of 100 mg/kg (estimated exposure was approximately 20 times the AUC for adults at the maximum recommended daily oral dose). Montelukast had no effects on fertility in male rats at oral doses up to 800 mg/kg (estimated exposure was approximately 160 times the AUC for adults at the maximum recommended daily oral dose).

Pregnancy Category B

No teratogenicity was observed in rats at oral doses up to 400 mg/kg/day (estimated exposure was approximately 100 times the AUC for adults at the maximum recommended daily oral dose) and in rabbits at oral doses up to 300 mg/kg/day (estimated exposure was approximately 110 times the AUC for adults at the maximum recommended daily oral dose). Montelukast crosses the placenta following oral dosing in rats and rabbits. There are, however, no adequate and well-controlled studies in pregnant women. Because animal reproduction studies are not always predictive of human response, SINGULAIR should be used during pregnancy only if clearly needed.

During worldwide marketing experience, congenital limb defects have been rarely reported in the offspring of women being treated with SINGULAIR during pregnancy. Most of these women were also taking other asthma medications during their pregnancy. A causal relationship between these events and SINGULAIR has not been established.

Merck & Co., Inc. maintains a registry to monitor the pregnancy outcomes of women exposed to SINGULAIR while pregnant. Healthcare providers are encouraged to report any prenatal exposure to SINGULAIR by calling the Pregnancy Registry at (800) 986-8999.

Nursing Mothers

Studies in rats have shown that montelukast is excreted in milk. It is not known if montelukast is excreted in human milk. Because many drugs are excreted in human milk, caution should be exercised when SINGULAIR is given to a nursing mother.

Pediatric Use

Safety and efficacy of SINGULAIR have been established in adequate and well-controlled studies in pediatric patients with asthma 6 to 14 years of age. Safety and efficacy profiles in this age group are similar to those seen in adults. (See Clinical Studies and ADVERSE REACTIONS.)

The efficacy of SINGULAIR for the treatment of seasonal allergic rhinitis in pediatric patients 2 to 14 years of age and for the treatment of perennial allergic rhinitis in pediatric patients 6 months to 14 years of age is supported by extrapolation from the demonstrated efficacy in patients 15 years of age and older with allergic rhinitis as well as the assumption that the disease course, pathophysiology and the drug’s effect are substantially similar among these populations.

The safety of SINGULAIR 4-mg chewable tablets in pediatric patients 2 to 5 years of age with asthma has been demonstrated by adequate and well-controlled data (see ADVERSE REACTIONS). Efficacy of SINGULAIR in this age group is extrapolated from the demonstrated efficacy in patients 6 years of age and older with asthma and is based on similar pharmacokinetic data, as well as the assumption that the disease course, pathophysiology and the drug’s effect are substantially similar among these populations. Efficacy in this age group is supported by exploratory efficacy assessments from a large, well-controlled safety study conducted in patients 2 to 5 years of age.

The safety of SINGULAIR 4-mg oral granules in pediatric patients 12 to 23 months of age with asthma has been demonstrated in an analysis of 172 pediatric patients, 124 of whom were treated with SINGULAIR, in a 6-week, double-blind, placebo-controlled study (see ADVERSE REACTIONS). Efficacy of SINGULAIR in this age group is extrapolated from the demonstrated efficacy in patients 6 years of age and older with asthma based on similar mean systemic exposure (AUC), and that the disease course, pathophysiology and the drug’s effect are substantially similar among these populations, supported by efficacy data from a safety trial in which efficacy was an exploratory assessment.

The safety of SINGULAIR 4-mg and 5-mg chewable tablets in pediatric patients aged 2 to 14 years with allergic rhinitis is supported by data from studies conducted in pediatric patients aged 2 to 14 years with asthma. A safety study in pediatric patients 2 to 14 years of age with seasonal allergic rhinitis demonstrated a similar safety profile (see ADVERSE REACTIONS). The safety of SINGULAIR 4-mg oral granules in pediatric patients as young as 6 months of age with perennial allergic rhinitis is supported by extrapolation from safety data obtained from studies conducted in pediatric patients 6 months to 23 months of age with asthma and from pharmacokinetic data comparing systemic exposures in patients 6 months to 23 months of age to systemic exposures in adults.

The safety and effectiveness in pediatric patients below the age of 12 months with asthma and 6 months with perennial allergic rhinitis have not been established.

Geriatric Use

Of the total number of subjects in clinical studies of montelukast, 3.5% were 65 years of age and over, and 0.4% were 75 years of age and over. No overall differences in safety or effectiveness were observed between these subjects and younger subjects, and other reported clinical experience has not identified differences in responses between the elderly and younger patients, but greater sensitivity of some older individuals cannot be ruled out.

ADVERSE REACTIONS

Adults and Adolescents 15 Years of Age and Older with Asthma

SINGULAIR has been evaluated for safety in approximately 2950 adult and adolescent patients 15 years of age and older in clinical trials. In placebo-controlled clinical trials, the following adverse experiences reported with SINGULAIR occurred in greater than or equal to 1% of patients and at an incidence greater than that in patients treated with placebo, regardless of causality assessment:

Adverse Experiences Occurring in ≥1% of Patients with an Incidence Greater than that in Patients Treated with Placebo, Regardless of Causality Assessment
 | SINGULAIR 10 mg/day (%) (n=1955) | Placebo (%) (n=1180)
Body As A Whole Asthenia/fatigue Fever Pain, abdominal Trauma | 1.8 1.5 2.9 1.0 | 1.2 0.9 2.5 0.8
Digestive System Disorders Dyspepsia Gastroenteritis, infectious Pain, dental | 2.1 1.5 1.7 | 1.1 0.5 1.0
Nervous System/Psychiatric Dizziness Headache | 1.9 18.4 | 1.4 18.1
Respiratory System Disorders Congestion, nasal Cough Influenza | 1.6 2.7 4.2 | 1.3 2.4 3.9
Skin/Skin Appendages Disorder Rash | 1.6 | 1.2
Laboratory Adverse Experiences [Number of patients tested (SINGULAIR and placebo, respectively): ALT and AST, 1935, 1170; pyuria, 1924, 1159.] ALT increased AST increased Pyuria | 2.1 1.6 1.0 | 2.0 1.2 0.9

The frequency of less common adverse events was comparable between SINGULAIR and placebo.

The safety profile of SINGULAIR when administered as a single dose for prevention of EIB in adult and adolescent patients 15 years of age and older was consistent with the safety profile previously described for SINGULAIR.

Cumulatively, 569 patients were treated with SINGULAIR for at least 6 months, 480 for one year, and 49 for two years in clinical trials. With prolonged treatment, the adverse experience profile did not significantly change.

Pediatric Patients 6 to 14 Years of Age with Asthma

SINGULAIR has been evaluated for safety in 476 pediatric patients 6 to 14 years of age. Cumulatively, 289 pediatric patients were treated with SINGULAIR for at least 6 months, and 241 for one year or longer in clinical trials. The safety profile of SINGULAIR in the 8-week, double-blind, pediatric efficacy trial was generally similar to the adult safety profile. In pediatric patients 6 to 14 years of age receiving SINGULAIR, the following events occurred with a frequency ≥2% and more frequently than in pediatric patients who received placebo, regardless of causality assessment: pharyngitis, influenza, fever, sinusitis, nausea, diarrhea, dyspepsia, otitis, viral infection, and laryngitis. The frequency of less common adverse events was comparable between SINGULAIR and placebo. With prolonged treatment, the adverse experience profile did not significantly change.

In studies evaluating growth rate, the safety profile in these pediatric patients was consistent with the safety profile previously described for SINGULAIR. In a 56-week, double-blind study evaluating growth rate in pediatric patients 6 to 8 years of age receiving SINGULAIR, the following events not previously observed with the use of SINGULAIR in this age group occurred with a frequency ≥2% and more frequently than in pediatric patients who received placebo, regardless of causality assessment: headache, rhinitis (infective), varicella, gastroenteritis, atopic dermatitis, acute bronchitis, tooth infection, skin infection, and myopia.

Pediatric Patients 2 to 5 Years of Age with Asthma

SINGULAIR has been evaluated for safety in 573 pediatric patients 2 to 5 years of age in single- and multiple-dose studies. Cumulatively, 426 pediatric patients 2 to 5 years of age were treated with SINGULAIR for at least 3 months, 230 for 6 months or longer, and 63 patients for one year or longer in clinical trials. SINGULAIR 4 mg administered once daily at bedtime was generally well tolerated in clinical trials. In pediatric patients 2 to 5 years of age receiving SINGULAIR, the following events occurred with a frequency ≥2% and more frequently than in pediatric patients who received placebo, regardless of causality assessment: fever, cough, abdominal pain, diarrhea, headache, rhinorrhea, sinusitis, otitis, influenza, rash, ear pain, gastroenteritis, eczema, urticaria, varicella, pneumonia, dermatitis, and conjunctivitis.

Pediatric Patients 6 to 23 Months of Age with Asthma

Safety and effectiveness in pediatric patients younger than 12 months of age with asthma have not been established.

SINGULAIR has been evaluated for safety in 175 pediatric patients 6 to 23 months of age. The safety profile of SINGULAIR in a 6-week, double-blind, placebo-controlled clinical study was generally similar to the safety profile in adults and pediatric patients 2 to 14 years of age. SINGULAIR administered once daily at bedtime was generally well tolerated. In pediatric patients 6 to 23 months of age receiving SINGULAIR, the following events occurred with a frequency ≥2% and more frequently than in pediatric patients who received placebo, regardless of causality assessment: upper respiratory infection, wheezing; otitis media; pharyngitis, tonsillitis, cough; and rhinitis. The frequency of less common adverse events was comparable between SINGULAIR and placebo.

Adults and Adolescents 15 Years of Age and Older with Seasonal Allergic Rhinitis

SINGULAIR has been evaluated for safety in 2199 adult and adolescent patients 15 years of age and older in clinical trials. SINGULAIR administered once daily in the morning or in the evening was generally well tolerated with a safety profile similar to that of placebo. In placebo-controlled clinical trials, the following event was reported with SINGULAIR with a frequency ≥1% and at an incidence greater than placebo, regardless of causality assessment: upper respiratory infection, 1.9% of patients receiving SINGULAIR vs. 1.5% of patients receiving placebo. In a 4-week, placebo-controlled clinical study, the safety profile was consistent with that observed in 2-week studies. The incidence of somnolence was similar to that of placebo in all studies.

Pediatric Patients 2 to 14 Years of Age with Seasonal Allergic Rhinitis

SINGULAIR has been evaluated in 280 pediatric patients 2 to 14 years of age in a 2-week, multicenter, double-blind, placebo-controlled, parallel-group safety study. SINGULAIR administered once daily in the evening was generally well tolerated with a safety profile similar to that of placebo. In this study, the following events occurred with a frequency ≥2% and at an incidence greater than placebo, regardless of causality assessment: headache, otitis media, pharyngitis, and upper respiratory infection.

Adults and Adolescents 15 Years of Age and Older with Perennial Allergic Rhinitis

SINGULAIR has been evaluated for safety in 3357 adult and adolescent patients 15 years of age and older with perennial allergic rhinitis of whom 1632 received SINGULAIR in two, 6-week, clinical studies. SINGULAIR administered once daily was generally well tolerated, with a safety profile consistent with that observed in patients with seasonal allergic rhinitis and similar to that of placebo. In these two studies, the following events were reported with SINGULAIR with a frequency ≥1% and at an incidence greater than placebo, regardless of causality assessment: sinusitis, upper respiratory infection, sinus headache, cough, epistaxis, and increased ALT. The incidence of somnolence was similar to that of placebo.

Pediatric Patients 6 Months to 14 Years of Age with Perennial Allergic Rhinitis

The safety in patients 2 to 14 years of age with perennial allergic rhinitis is supported by the established safety in patients 2 to 14 years of age with seasonal allergic rhinitis. The safety in patients 6 to 23 months of age is supported by data from pharmacokinetic and safety and efficacy studies in asthma in this pediatric population and from adult pharmacokinetic studies.

Post-Marketing Experience

The following additional adverse reactions have been reported in post-marketing use:

Blood and lymphatic system disorders: increased bleeding tendency

Immune system disorders: hypersensitivity reactions including anaphylaxis, very rarely hepatic eosinophilic infiltration

Psychiatric disorders: agitation including aggressive behavior or hostility, anxiousness, depression, dream abnormalities, hallucinations, insomnia, irritability, restlessness, somnambulism, suicidal thinking and behavior (including suicide), tremor (see PRECAUTIONS, Neuropsychiatric Events)

Nervous system disorders: drowsiness, paraesthesia/hypoesthesia, seizures

Cardiac disorders: palpitations

Respiratory, thoracic and mediastinal disorders: epistaxis

Gastrointestinal disorders: diarrhea, dyspepsia, nausea, very rarely pancreatitis, vomiting

Hepatobiliary disorders: Rare cases of cholestatic hepatitis, hepatocellular liver-injury, and mixed-pattern liver injury have been reported in patients treated with SINGULAIR. Most of these occurred in combination with other confounding factors, such as use of other medications, or when SINGULAIR was administered to patients who had underlying potential for liver disease such as alcohol use or other forms of hepatitis.

Skin and subcutaneous tissue disorders: angioedema, bruising, erythema nodosum, pruritus, urticaria

Musculoskeletal and connective tissue disorders: arthralgia, myalgia including muscle cramps

General disorders and administration site conditions: edema

In rare cases, patients with asthma on therapy with SINGULAIR may present with systemic eosinophilia, sometimes presenting with clinical features of vasculitis consistent with Churg-Strauss syndrome, a condition which is often treated with systemic corticosteroid therapy. These events usually, but not always, have been associated with the reduction of oral corticosteroid therapy. Physicians should be alert to eosinophilia, vasculitic rash, worsening pulmonary symptoms, cardiac complications, and/or neuropathy presenting in their patients. A causal association between SINGULAIR and these underlying conditions has not been established (see PRECAUTIONS, Eosinophilic Conditions).

OVERDOSAGE

No mortality occurred following single oral doses of montelukast up to 5000 mg/kg in mice (estimated exposure was approximately 335 and 210 times the AUC for adults and children, respectively, at the maximum recommended daily oral dose) and rats (estimated exposure was approximately 230 and 145 times the AUC for adults and children, respectively, at the maximum recommended daily oral dose).

No specific information is available on the treatment of overdosage with SINGULAIR. In chronic asthma studies, montelukast has been administered at doses up to 200 mg/day to adult patients for 22 weeks and, in short-term studies, up to 900 mg/day to patients for approximately a week without clinically important adverse experiences. In the event of overdose, it is reasonable to employ the usual supportive measures; e.g., remove unabsorbed material from the gastrointestinal tract, employ clinical monitoring, and institute supportive therapy, if required.

There have been reports of acute overdosage in post-marketing experience and clinical studies with SINGULAIR. These include reports in adults and children with a dose as high as 1000 mg. The clinical and laboratory findings observed were consistent with the safety profile in adults and pediatric patients. There were no adverse experiences in the majority of overdosage reports. The most frequently occurring adverse experiences were consistent with the safety profile of SINGULAIR and included abdominal pain, somnolence, thirst, headache, vomiting and psychomotor hyperactivity.

It is not known whether montelukast is removed by peritoneal dialysis or hemodialysis.

DOSAGE AND ADMINISTRATION

Dosage Information

The dosage for adults and adolescents 15 years of age and older is one 10-mg tablet.

The dosage for pediatric patients 6 to 14 years of age is one 5-mg chewable tablet.

The dosage for pediatric patients 2 to 5 years of age is one 4-mg chewable tablet or one packet of 4-mg oral granules.

The dosage for pediatric patients 6 to 23 months of age is one packet of 4-mg oral granules.

Asthma in Patients 12 Months of Age and Older

SINGULAIR should be taken once daily in the evening. Safety and effectiveness in pediatric patients less than 12 months of age have not been established.

Exercise-Induced Bronchoconstriction (EIB) in Patients 15 Years of Age and Older:

For prevention of EIB, a single dose of SINGULAIR should be taken at least 2 hours before exercise. An additional dose of SINGULAIR should not be taken within 24 hours of a previous dose. Patients already taking one tablet daily for another indication (including chronic asthma) should not take an additional dose to prevent EIB. All patients should have available for rescue a short-acting β-agonist. Safety and effectiveness in patients younger than 15 years of age have not been established. Daily administration of SINGULAIR for the chronic treatment of asthma has not been established to prevent acute episodes of exercise-induced bronchoconstriction.

Perennial Allergic Rhinitis in Patients 6 Months and Older

For allergic rhinitis SINGULAIR should be taken once daily. The time of administration may be individualized to suit patient needs.

Safety and effectiveness in pediatric patients younger than 2 years of age with seasonal allergic rhinitis and less than 6 months of age with perennial allergic rhinitis have not been established.

Asthma and Allergic Rhinitis in Patients 12 Months of Age and Older:

Patients with both asthma and allergic rhinitis should take only one tablet daily in the evening.

Administration of SINGULAIR Oral Granules

SINGULAIR 4-mg oral granules can be administered either directly in the mouth, dissolved in 1 teaspoonful (5 mL) of cold or room temperature baby formula or breast milk, or mixed with a spoonful of cold or room temperature soft foods; based on stability studies, only applesauce, carrots, rice, or ice cream should be used. The packet should not be opened until ready to use. After opening the packet, the full dose (with or without mixing with baby formula, breast milk, or food) must be administered within 15 minutes. If mixed with baby formula, breast milk, or food, SINGULAIR oral granules must not be stored for future use. Discard any unused portion. SINGULAIR oral granules are not intended to be dissolved in any liquid other than baby formula or breast milk for administration. However, liquids may be taken subsequent to administration. SINGULAIR oral granules can be administered without regard to the time of meals.

HOW SUPPLIED

No. 3841 — SINGULAIR Oral Granules, 4 mg, are white granules with 500 mg net weight, packed in a child-resistant foil packet.

No. 3796 — SINGULAIR Tablets, 4 mg, are pink, oval, bi-convex-shaped chewable tablets, with code MRK 711 on one side and SINGULAIR on the other.

No. 3760 — SINGULAIR Tablets, 5 mg, are pink, round, bi-convex-shaped chewable tablets, with code MRK 275 on one side and SINGULAIR on the other.

No. 3761 — SINGULAIR Tablets, 10 mg, are beige, rounded square-shaped, film-coated tablets, with code MRK 117 on one side and SINGULAIR on the other.

They are supplied by Dispensing Solutions Inc. as follows:

NDC | Strength | Quantity/Form | Color | Source NDC
68258-3032-03 | 5 mg | 30 TABLET | pink | 0006-0275-31
68258-3033-03 | 10 mg | 30 TABLET | beige | 0006-0117-31

This product was Manufactured By:

MERCK SHARP & DOHME LTD.
Cramlington, Northumberland, UK NE23 3JU
Distributed by:
MERCK & CO., INC.
Whitehouse Station, NJ 08889, USA

And Repackaged By:

Dispensing Solutions Inc.
3000 West Warner Ave
Santa Ana, CA 92704
United States

Storage

Store SINGULAIR 4-mg oral granules, 4-mg chewable tablets, 5-mg chewable tablets and 10-mg film-coated tablets at 25°C (77°F), excursions permitted to 15-30°C (59-86°F) [see USP Controlled Room Temperature]. Protect from moisture and light. Store in original package.

Storage for Bulk Bottles

Store bottles of 1000 SINGULAIR 5-mg chewable tablets and 8000 SINGULAIR 10-mg film-coated tablets at 25°C (77°F), excursions permitted to 15-30°C (59-86°F) [see USP Controlled Room Temperature]. Protect from moisture and light. Store in original container. When product container is subdivided, repackage into a well-closed, light resistant container.

PATIENT PACKAGE INSERT

Patient Information
SINGULAIR® (SING-u-lair) Tablets, Chewable Tablets, and Oral Granules
Generic name: montelukast (mon-te-LOO-kast) sodium

Read this information before you start taking SINGULAIR®. Also, read the leaflet you get each time you refill SINGULAIR, since there may be new information in the leaflet since the last time you saw it. This leaflet does not take the place of talking with your doctor about your medical condition and/or your treatment.

What is SINGULAIR^1?

- SINGULAIR is a medicine called a leukotriene receptor antagonist. It works by blocking substances in the body called leukotrienes. Blocking leukotrienes improves asthma and allergic rhinitis. SINGULAIR is not a steroid. Studies have shown that SINGULAIR does not affect the growth rate of children. (See the end of this leaflet for more information about asthma and allergic rhinitis.)

SINGULAIR is prescribed for the treatment of asthma, the prevention of exercise-induced asthma, and allergic rhinitis:

1. Asthma.
  SINGULAIR should be used for the long-term management of asthma in adults and children ages 12 months and older.
  Do not take SINGULAIR for the immediate relief of an asthma attack. If you get an asthma attack, you should follow the instructions your doctor gave you for treating asthma attacks.
2. Prevention of exercise-induced asthma.
  SINGULAIR is used for the prevention of exercise-induced asthma in patients 15 years of age and older.
3. Allergic Rhinitis.
  SINGULAIR is used to help control the symptoms of allergic rhinitis (sneezing, stuffy nose, runny nose, itching of the nose). SINGULAIR is used to treat seasonal allergic rhinitis (outdoor allergies that happen part of the year) in adults and children ages 2 years and older, and perennial allergic rhinitis (indoor allergies that happen all year) in adults and children ages 6 months and older.

Who should not take SINGULAIR?

Do not take SINGULAIR if you are allergic to SINGULAIR or any of its ingredients.

The active ingredient in SINGULAIR is montelukast sodium.

See the end of this leaflet for a list of all the ingredients in SINGULAIR.

What should I tell my doctor before I start taking SINGULAIR?

Tell your doctor about:

- Pregnancy: If you are pregnant or plan to become pregnant, SINGULAIR may not be right for you.
- Breast-feeding: If you are breast-feeding, SINGULAIR may be passed in your milk to your baby. You should consult your doctor before taking SINGULAIR if you are breast-feeding or intend to breast-feed.
- Medical Problems or Allergies: Talk about any medical problems or allergies you have now or had in the past.
- Other Medicines: Tell your doctor about all the medicines you take, including prescription and non-prescription medicines, and herbal supplements. Some medicines may affect how SINGULAIR works, or SINGULAIR may affect how your other medicines work.

How should I take SINGULAIR?

For adults and children 12 months of age and older with asthma:

- Take SINGULAIR once a day in the evening.
- Take SINGULAIR every day for as long as your doctor prescribes it, even if you have no asthma symptoms.
- You may take SINGULAIR with food or without food.
- If your asthma symptoms get worse, or if you need to increase the use of your inhaled rescue medicine for asthma attacks, call your doctor right away.
- Do not take SINGULAIR for the immediate relief of an asthma attack. If you get an asthma attack, you should follow the instructions your doctor gave you for treating asthma attacks.
- Always have your inhaled rescue medicine for asthma attacks with you.
- Do not stop taking or lower the dose of your other asthma medicines unless your doctor tells you to.

For patients 15 years of age and older for the prevention of exercise-induced asthma:

- Take SINGULAIR at least 2 hours before exercise.
- Always have your inhaled rescue medicine for asthma attacks with you.
- If you are taking SINGULAIR daily for chronic asthma or allergic rhinitis, do not take an additional dose to prevent exercise-induced asthma. Speak to your doctor about your treatment of exercise-induced asthma.
- Do not take an additional dose of SINGULAIR within 24 hours of a previous dose.

For adults and children 2 years of age and older with seasonal allergic rhinitis, or for adults and children 6 months of age and older with perennial allergic rhinitis:

- Take SINGULAIR once a day, at about the same time each day.
- Take SINGULAIR every day for as long as your doctor prescribes it.
- You may take SINGULAIR with food or without food.

How should I give SINGULAIR oral granules to my child?

Do not open the packet until ready to use.

SINGULAIR 4-mg oral granules can be given:

- directly in the mouth;
- dissolved in 1 teaspoonful (5 mL) of cold or room temperature baby formula or breast milk;
- mixed with a spoonful of one of the following soft foods at cold or room temperature: applesauce, mashed carrots, rice, or ice cream.

Be sure that the entire dose is mixed with the food, baby formula, or breast milk and that the child is given the entire spoonful of the food, baby formula, or breast milk mixture right away (within 15 minutes).

IMPORTANT: Never store any oral granules mixed with food, baby formula, or breast milk for use at a later time. Throw away any unused portion.

Do not put SINGULAIR oral granules in any liquid drink other than baby formula or breast milk. However, your child may drink liquids after swallowing the SINGULAIR oral granules.

What is the dose of SINGULAIR?

For asthma -Take once daily in the evening:

- One 10-mg tablet for adults and adolescents 15 years of age and older,
- One 5-mg chewable tablet for children 6 to 14 years of age,
- One 4-mg chewable tablet or one packet of 4-mg oral granules for children 2 to 5 years of age, or
- One packet of 4-mg oral granules for children 12 to 23 months of age.

For exercise-induced asthma - Take at least 2 hours before exercise, but not more than once daily:

- One 10-mg tablet for adults and adolescents 15 years of age and older.

For allergic rhinitis -Take once daily at about the same time each day:

- One 10-mg tablet for adults and adolescents 15 years of age and older,
- One 5-mg chewable tablet for children 6 to 14 years of age,
- One 4-mg chewable tablet for children 2 to 5 years of age, or
- One packet of 4-mg oral granules for children 2 to 5 years of age with seasonal allergic rhinitis, or for children 6 months to 5 years of age with perennial allergic rhinitis.

What should I avoid while taking SINGULAIR?

If you have asthma and if your asthma is made worse by aspirin, continue to avoid aspirin or other medicines called non-steroidal anti-inflammatory drugs while taking SINGULAIR.

What are the possible side effects of SINGULAIR?

The side effects of SINGULAIR are usually mild, and generally did not cause patients to stop taking their medicine. The side effects in patients treated with SINGULAIR were similar in type and frequency to side effects in patients who were given a placebo (a pill containing no medicine).

The most common side effects with SINGULAIR include:

- stomach pain
- stomach or intestinal upset
- heartburn
- tiredness
- fever
- stuffy nose
- cough
- flu
- upper respiratory infection
- dizziness
- headache
- rash

Less common side effects that have happened with SINGULAIR include:

- increased bleeding tendency
- allergic reactions [including swelling of the face, lips, tongue, and/or throat (which may cause trouble breathing or swallowing), hives and itching]
- drowsiness, pins and needles/numbness, seizures (convulsions or fits)
- palpitations
- nose bleed
- diarrhea, indigestion, inflammation of the pancreas, nausea, vomiting
- hepatitis
- bruising
- joint pain, muscle aches and muscle cramps
- swelling

Behavior and mood-related changes have been reported: agitation including aggressive behavior or hostility, bad/vivid dreams, depression, feeling anxious, hallucinations (seeing things that are not there), irritability, restlessness, sleep walking, suicidal thoughts and actions (including suicide), tremor, trouble sleeping. Tell your doctor if you experience behavior or mood-related changes while taking SINGULAIR.

Rarely, asthmatic patients taking SINGULAIR have experienced a condition that includes certain symptoms that do not go away or that get worse. These occur usually, but not always, in patients who were taking steroid pills by mouth for asthma and those steroids were being slowly lowered or stopped. Although SINGULAIR has not been shown to cause this condition, you must tell your doctor right away if you get one or more of these symptoms:

- a feeling of pins and needles or numbness of arms or legs
- a flu-like illness
- rash
- severe inflammation (pain and swelling) of the sinuses (sinusitis)

These are not all the possible side effects of SINGULAIR. For more information ask your doctor or pharmacist.

Talk to your doctor if you think you have side effects from taking SINGULAIR.

General Information about the safe and effective use of SINGULAIR

Medicines are sometimes prescribed for conditions that are not mentioned in patient information leaflets. Do not use SINGULAIR for a condition for which it was not prescribed. Do not give SINGULAIR to other people even if they have the same symptoms you have. It may harm them. Keep SINGULAIR and all medicines out of the reach of children.

Store SINGULAIR at 25°C (77°F). Protect from moisture and light. Store in original package.

This leaflet summarizes information about SINGULAIR. If you would like more information, talk to your doctor. You can ask your pharmacist or doctor for information about SINGULAIR that is written for health professionals.

What are the ingredients in SINGULAIR?

Active ingredient: montelukast sodium

SINGULAIR chewable tablets contain aspartame, a source of phenylalanine.
Phenylketonurics: SINGULAIR 4-mg and 5-mg chewable tablets contain 0.674 and 0.842 mg phenylalanine, respectively.

Inactive ingredients:

- 4-mg oral granules: mannitol, hydroxypropyl cellulose, and magnesium stearate.
- 4-mg and 5-mg chewable tablets: mannitol, microcrystalline cellulose, hydroxypropyl cellulose, red ferric oxide, croscarmellose sodium, cherry flavor, aspartame, and magnesium stearate.
- 10-mg tablet: microcrystalline cellulose, lactose monohydrate, croscarmellose sodium, hydroxypropyl cellulose, magnesium stearate, hydroxypropyl methylcellulose, titanium dioxide, red ferric oxide, yellow ferric oxide, and carnauba wax.

What is asthma?

Asthma is a continuing (chronic) inflammation of the bronchial passageways which are the tubes that carry air from outside the body to the lungs.

Symptoms of asthma include:

- coughing
- wheezing
- chest tightness
- shortness of breath

What is exercise-induced asthma?

Exercise-induced asthma, more accurately called exercise-induced bronchoconstriction occurs when exercise triggers symptoms of asthma.

What is allergic rhinitis?

- Seasonal allergic rhinitis, also known as hay fever, is triggered by outdoor allergens such as pollens from trees, grasses, and weeds.
- Perennial allergic rhinitis may occur year-round and is generally triggered by indoor allergens such as dust mites, animal dander, and/or mold spores.
- Symptoms of allergic rhinitis may include:
  - stuffy, runny, and/or itchy nose
  - sneezing

Rx only

PRINCIPAL DISPLAY PANEL - CHEWABLE TABLETS - BOTTLE LABEL - 5 mg

Singulair® 5 mg
(Montelukast Sodium) CHEWABLE TABLETS
For Pediatric Patients 6-14 Years of Age

Phenylketonurics: contains phenylalanine (a component of aspartame) 0.842 mg per 5-mg chewable tablet. Each tablet contains 5.2 mg Montelukast Sodium equivalent to 5 mg Montelukast.

30 Tablets

NDC 68258-3032-03

Store at 25°C (77°F), excursions permitted to 15-30°C (59-86°F) [see USP Controlled Room Temperature]. Protect from moisture and light.
Store in original package.

USUAL DOSAGE: See accompanying circular.

Keep this and all drugs out of the reach of children

Rx only

PRINCIPAL DISPLAY PANEL - TABLETS - BOTTLE LABEL - 10 mg

Singulair® 10 mg
(Montelukast Sodium) TABLETS
For Adults 15 Years of Age and Older

Each tablet contains 10.4 mg Montelukast Sodium equivalent to 10 mg Montelukast.

30 Tablets

NDC 68258-3033-03

Store at 25°C (77°F), excursions permitted to 15-30°C (59-86°F) [see USP Controlled Room Temperature]. Protect from moisture and light.
Store in original package.

USUAL DOSAGE: See accompanying circular.

Rx only